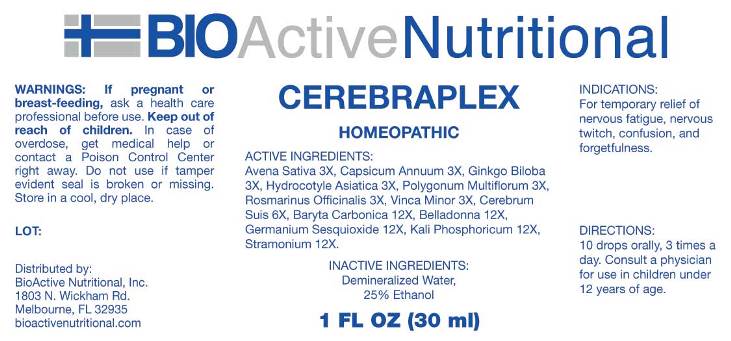 DRUG LABEL: Cerebraplex
NDC: 43857-0398 | Form: LIQUID
Manufacturer: BioActive Nutritional, Inc.
Category: homeopathic | Type: HUMAN OTC DRUG LABEL
Date: 20160606

ACTIVE INGREDIENTS: AVENA SATIVA FLOWERING TOP 3 [hp_X]/1 mL; CAPSICUM 3 [hp_X]/1 mL; GINKGO 3 [hp_X]/1 mL; CENTELLA ASIATICA 3 [hp_X]/1 mL; FALLOPIA MULTIFLORA ROOT 3 [hp_X]/1 mL; ROSMARINUS OFFICINALIS FLOWERING TOP 3 [hp_X]/1 mL; VINCA MINOR 3 [hp_X]/1 mL; SUS SCROFA CEREBRUM 6 [hp_X]/1 mL; BARIUM CARBONATE 12 [hp_X]/1 mL; ATROPA BELLADONNA 12 [hp_X]/1 mL; GERMANIUM SESQUIOXIDE 12 [hp_X]/1 mL; POTASSIUM PHOSPHATE, DIBASIC 12 [hp_X]/1 mL; DATURA STRAMONIUM 12 [hp_X]/1 mL
INACTIVE INGREDIENTS: WATER; ALCOHOL

Drug Facts:

ACTIVE INGREDIENTS:

Avena Sativa 3X, Capsicum Annuum 3X, Ginkgo Biloba 3X, Hydrocotyle Asiatica 3X, Polygonum Multiflorum 3X, Rosmarinus Officinalis 3X, Vinca Minor 3X, Cerebrum Suis 6X, Baryta Carbonica 12X, Belladonna 12X, Germanium Sesquioxide 12X, Kali Phosphoricum 12X, Stramonium 12X.

INDICATIONS:

For temporary relief of nervous fatigue, nervous twitch, confusion, and forgetfulness.

WARNINGS:

If pregnant or breast-feeding, ask a health care professional before use.

Keep out of reach of children. In case of overdose, get medical help or contact a Poison Control Center right away.

Do not use if tamper evident seal is broken or missing.

Store in a cool, dry place.

Keep out of reach of children. In case of overdose, get medical help or contact a Poison Control Center right away.

DIRECTIONS:

10 drops orally, 3 times a day. Consult a physician for use in children under 12 years of age.

INACTIVE INGREDIENTS:

Demineralized Water, 25% Ethanol

INDICATIONS:

For temporary relief of nervous fatigue, nervous twitch, confusion, and forgetfulness.

QUESTIONS:

Distributed by:

BioActiveNutritional, Inc.

1803 N. Wickham Rd.

Melbourne, FL 32935

bioactivenutrtional.com

PACKAGE DISPLAY LABEL:

BIOActive Nutritional

CEREBRAPLEX

HOMEOPATHIC

1 FL OZ (30 mL)